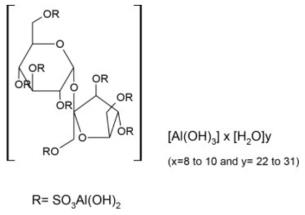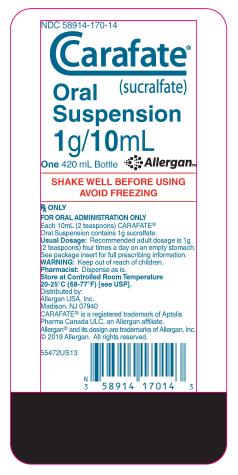 DRUG LABEL: Carafate
NDC: 58914-170 | Form: SUSPENSION
Manufacturer: Allergan, Inc.
Category: prescription | Type: HUMAN PRESCRIPTION DRUG LABEL
Date: 20230608

ACTIVE INGREDIENTS: SUCRALFATE 1 g/10 mL
INACTIVE INGREDIENTS: SILICON DIOXIDE; FD&C RED NO. 40 0.004 mg/10 mL; GLYCERIN 87.92 mg/10 mL; METHYLCELLULOSE, UNSPECIFIED; METHYLPARABEN 1.78 mg/10 mL; MICROCRYSTALLINE CELLULOSE; WATER 618.006 mg/10 mL; SORBITOL SOLUTION 177.62 mg/10 mL

CARAFATE®
(sucralfate)
Oral Suspension

DESCRIPTION

CARAFATE Oral Suspension contains sucralfate and sucralfate is an α-D-glucopyranoside, β-D- fructofuranosyl-, octakis-(hydrogen sulfate), aluminum complex.

CARAFATE Oral Suspension for oral administration contains 1 g of sucralfate per 10 mL. CARAFATE Oral Suspension also contains: colloidal silicon dioxide NF, FD&C Red #40, flavor, glycerin USP, methylcellulose USP, methylparaben NF, microcrystalline cellulose NF, purified water USP, simethicone emulsion USP, and sorbitol solution USP. Therapeutic category: antiulcer.

CLINICAL PHARMACOLOGY

Sucralfate is only minimally absorbed from the gastrointestinal tract. The small amounts of the sulfated disaccharide that are absorbed are excreted primarily in the urine.

Although the mechanism of sucralfate’s ability to accelerate healing of duodenal ulcers remains to be fully defined, it is known that it exerts its effect through a local, rather than systemic, action. The following observations also appear pertinent:

1. Studies in human subjects and with animal models of ulcer disease have shown that sucralfate forms an ulcer-adherent complex with proteinaceous exudate at the ulcer site.
2. In vitro, a sucralfate-albumin film provides a barrier to diffusion of hydrogen ions.
3. In human subjects, sucralfate given in doses recommended for ulcer therapy inhibits pepsin activity in gastric juice by 32%.

In vitro, sucralfate adsorbs bile salts.

These observations suggest that sucralfate’s antiulcer activity is the result of formation of an ulcer- adherent complex that covers the ulcer site and protects it against further attack by acid, pepsin, and bile salts. There are approximately 14 to 16 mEq of acid-neutralizing capacity per 1 g dose of sucralfate.

CLINICAL TRIALS

In a multicenter, double-blind, placebo-controlled study of CARAFATE Oral Suspension, a dosage regimen of 1 gram (10 mL) four times daily was demonstrated to be superior to placebo in ulcer healing.

Results From Clinical Trials Healing Rates for Acute Duodenal
Ulcer
Treatment | n | Week 2 Healing Rates | Week 4 Healing Rates | Week 8 Healing Rates
CARAFATE Oral Suspension | 145 | 23(16%)* | 66(46%)† | 95(66%)‡
Placebo | 147 | 10(7%) | 39(27%) | 58(39%)

*P=0.016 †P=0.001 ‡P=0.0001

Equivalence of sucralfate oral suspension to sucralfate tablets has not been demonstrated.

INDICATIONS AND USAGE

CARAFATE (sucralfate) Oral Suspension is indicated in the short-term (up to 8 weeks) treatment of active duodenal ulcer.

CONTRAINDICATIONS

CARAFATE Oral Suspension is contraindicated for patients with known hypersensitivity reactions to the active substance or to any of the excipients.

WARNINGS

Fatal complications, including pulmonary and cerebral emboli have occurred with inappropriate intravenous administration of CARAFATE Oral Suspension. Administer CARAFATE Oral Suspension only by the oral route. Do not administer intravenously.

PRECAUTIONS

The physician should read the “PRECAUTIONS” section when considering the use of CARAFATE Oral Suspension in pregnant or pediatric patients, or patients of childbearing potential.

Duodenal ulcer is a chronic, recurrent disease. While short-term treatment with sucralfate can result in complete healing of the ulcer, a successful course of treatment with sucralfate should not be expected to alter the post healing frequency or severity of duodenal ulceration.

Episodes of hyperglycemia have been reported in diabetic patients. Close monitoring of glycemia in diabetic patients treated with CARAFATE Oral Suspension is recommended. Adjustment of the anti-diabetic treatment dose during the use of CARAFATE Oral Suspension might be necessary.

Special Populations: Chronic Renal Failure and Dialysis Patients

When sucralfate is administered orally, small amounts of aluminum are absorbed from the gastrointestinal tract. Concomitant use of sucralfate with other products that contain aluminum, such as aluminum-containing antacids, may increase the total body burden of aluminum. Patients with normal renal function receiving the recommended doses of sucralfate and aluminum- containing products adequately excrete aluminum in the urine. Patients with chronic renal failure or those receiving dialysis have impaired excretion of absorbed aluminum. In addition, aluminum does not cross dialysis membranes because it is bound to albumin and transferrin plasma proteins. Aluminum accumulation and toxicity (aluminum osteodystrophy, osteomalacia, encephalopathy) have been described in patients with renal impairment. Sucralfate should be used with caution in patients with chronic renal failure.

Drug Interactions

Some studies have shown that simultaneous sucralfate administration in healthy volunteers reduced the extent of absorption (bioavailability) of single doses of the following: cimetidine, digoxin, fluoroquinolone antibiotics, ketoconazole, l-thyroxine, phenytoin, quinidine, ranitidine, tetracycline, and theophylline. Subtherapeutic prothrombin times with concomitant warfarin and sucralfate therapy have been reported in spontaneous and published case reports. However, two clinical studies have demonstrated no change in either serum warfarin concentration or prothrombin time with the addition of sucralfate to chronic warfarin therapy.

The mechanism of these interactions appears to be nonsystemic in nature, presumably resulting from sucralfate binding to the concomitant agent in the gastrointestinal tract. In all cases studied to date (cimetidine, ciprofloxacin, digoxin, norfloxacin, ofloxacin, and ranitidine), dosing the concomitant medication 2 hours before sucralfate eliminated the interaction. Due to CARAFATE Oral Suspension’s potential to alter the absorption of some drugs, CARAFATE Oral Suspension should be administered separately from other drugs when alterations in bioavailability are felt to be critical. In these cases, patients should be monitored appropriately.

Carcinogenesis, Mutagenesis, Impairment of Fertility

Chronic oral toxicity studies of 24 months’ duration were conducted in mice and rats at doses up to 1 g/kg (12 times the human dose).

There was no evidence of drug-related tumorigenicity. A reproduction study in rats at doses up to 38 times the human dose did not reveal any indication of fertility impairment. Mutagenicity studies were not conducted.

Pregnancy

Teratogenic effects

Teratogenicity studies have been performed in mice, rats, and rabbits at doses up to 50 times the human dose and have revealed no evidence of harm to the fetus due to sucralfate. There are, however, no adequate and well-controlled studies in pregnant women. Because animal reproduction studies are not always predictive of human response, this drug should be used during pregnancy only if clearly needed.

Nursing Mothers

It is not known whether this drug is excreted in human milk. Because many drugs are excreted in human milk, caution should be exercised when sucralfate is administered to a nursing woman.

Pediatric Use

Safety and effectiveness in pediatric patients have not been established.

Geriatric Use

Clinical studies of CARAFATE Oral Suspension did not include sufficient numbers of subjects aged 65 and over to determine whether they respond differently from younger subjects. Other reported clinical experience has not identified differences in responses between the elderly and younger patients. In general, dose selection for an elderly patient should be cautious, usually starting at the low end of the dosing range, reflecting the greater frequency of decreased hepatic, renal, or cardiac function, and of concomitant disease or other drug therapy (See DOSAGE AND ADMINISTRATION).

This drug is known to be substantially excreted by the kidney, and the risk of toxic reactions to this drug may be greater in patients with impaired renal function (See PRECAUTIONS Special Populations: Chronic Renal Failure and Dialysis Patients). Because elderly patients are more likely to have decreased renal function, care should be taken in dose selection, and it may be useful to monitor renal function.

ADVERSE REACTIONS

Adverse reactions to sucralfate tablets in clinical trials were minor and only rarely led to discontinuation of the drug. In studies involving over 2700 patients treated with sucralfate, adverse effects were reported in 129 (4.7%).

Constipation was the most frequent complaint (2%). Other adverse effects reported in less than 0.5% of the patients are listed below by body system:

Gastrointestinal: diarrhea, dry mouth, flatulence, gastric discomfort, indigestion, nausea, vomiting

Dermatological: pruritus, rash

Nervous System: dizziness, insomnia, sleepiness, vertigo

Other: back pain, headache

Post-marketing cases of hypersensitivity have been reported with the use of sucralfate oral suspension, including anaphylactic reactions, dyspnea, lip swelling, edema of the mouth, pharyngeal edema, pruritus, rash, swelling of the face and urticaria.

Cases of bronchospasm, laryngeal edema and respiratory tract edema have been reported with an unknown oral formulation of sucralfate.

Cases of hyperglycemia have been reported with sucralfate.

Bezoars have been reported in patients treated with sucralfate. The majority of patients had underlying medical conditions that may predispose to bezoar formation (such as delayed gastric emptying) or were receiving concomitant enteral tube feedings.

OVERDOSAGE

Due to limited experience in humans with overdosage of sucralfate, no specific treatment recommendations can be given. Acute oral studies in animals, however, using doses up to 12 g/kg body weight, could not find a lethal dose. Sucralfate is only minimally absorbed from the gastrointestinal tract. Risks associated with acute overdosage should, therefore, be minimal. In rare reports describing sucralfate overdose, most patients remained asymptomatic. Those few reports where adverse events were described included symptoms of dyspepsia, abdominal pain, nausea, and vomiting.

DOSAGE AND ADMINISTRATION

Active Duodenal Ulcer: The recommended adult oral dosage for duodenal ulcer is 1 gram (10 mL) four times per day. CARAFATE Oral Suspension should be administered on an empty stomach.

Antacids may be prescribed as needed for relief of pain but should not be taken within one-half hour before or after CARAFATE Oral Suspension.

While healing with sucralfate may occur during the first week or two, treatment should be continued for 4 to 8 weeks unless healing has been demonstrated by x-ray or endoscopic examination.

Elderly: In general, dose selection for an elderly patient should be cautious, usually starting at the low end of the dosing range, reflecting the greater frequency of decreased hepatic, renal, or cardiac function, and of concomitant disease or other drug therapy (See PRECAUTIONS, Geriatric Use).

Call your doctor for medical advice about side effects. You may report side effects to AbbVie, Inc at 1-800-678-1605 or FDA at 1-800-FDA-1088 or www.fda.gov/medwatch.

HOW SUPPLIED

CARAFATE (sucralfate) Oral Suspension 1 g/10 mL is a pink suspension supplied in bottles of 420 mL (NDC 58914-170-14).

SHAKE WELL BEFORE USING. AVOID FREEZING.

Store at controlled room temperature 20-25°C (68-77°F) [see USP].

Rx Only

Prescribing Information rev. Jun 2023

Distributed by:
AbbVie, Inc.
North Chicago, IL 60064

CARAFATE and its design are trademarks of Aptalis Pharma Canada ULC, an AbbVie company.

© 2023 AbbVie. All rights reserved.

v2.1USPI0170

PRINCIPAL DISPLAY PANEL

NDC 58914-170-14
Carafate®
(sucralfate)
Oral
Suspension
1g/ 10mL

One 420 mL Bottle

Rx ONLY